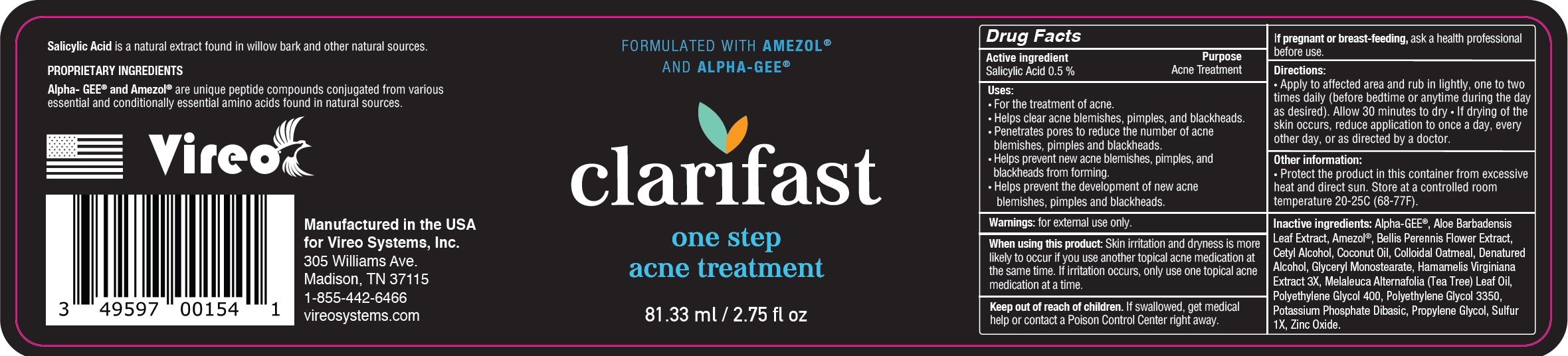 DRUG LABEL: CLARIFAST One Step Acne Treatment
NDC: 82908-358 | Form: CREAM
Manufacturer: VIREO SYSTEMS, INC.
Category: otc | Type: HUMAN OTC DRUG LABEL
Date: 20231111

ACTIVE INGREDIENTS: SALICYLIC ACID 5 mg/1 mL
INACTIVE INGREDIENTS: ALOE VERA LEAF; BELLIS PERENNIS FLOWER; CETYL ALCOHOL; COCONUT OIL; OATMEAL; GLYCERYL MONOSTEARATE; TEA TREE OIL; POLYETHYLENE GLYCOL 400; POLYETHYLENE GLYCOL 3350; DIBASIC POTASSIUM PHOSPHATE; PROPYLENE GLYCOL; ZINC OXIDE

CLARIFAST One Step Acne Treatment

Active ingredient

Salicylic Acid 0.5 %

Purpose

Acne Treatment

Uses:

• For the treatment of acne. • Helps clear acne blemishes, pimples, and blackheads. • Penetrates pores to reduce the number of acne blemishes, pimples and blackheads. • Helps prevent new acne blemishes, pimples, and blackheads from forming. • Helps prevent the development of new acne blemishes, pimples and blackheads.

Warnings:

for external use only.

When using this product:

Skin irritation and dryness is more likely to occur if you use another topical acne medication at the same time. If irritation occurs, only use one topical acne medication at a time.

Keep out of reach of children.

If swallowed, get medical help or contact a Poison Control Center right away.

If pregnant or breast-feeding,

ask a health professional before use.

Directions:

• Apply to affected area and rub in lightly, one to two times daily (before bedtime or anytime during the day as desired). Allow 30 minutes to dry • If drying of the skin occurs, reduce application to once a day, every other day, or as directed by a doctor.

Other information:

• Protect the product in this container from excessive heat and direct sun. Store at a controlled room temperature 20-25C (68-77F).

Inactive ingredients:

Alpha-GEE®, Aloe Barbadensis Leaf Extract, Amezol®, Bellis Perennis Flower Extract, Cetyl Alcohol, Coconut Oil, Colloidal Oatmeal, Denatured Alcohol, Glyceryl Monostearate, Hamamelis Virginiana Extract 3X, Melaleuca Alternafolia (Tea Tree) Leaf Oil, Polyethylene Glycol 400, Polyethylene Glycol 3350, Potassium Phosphate Dibasic, Propylene Glycol, Sulfur 1X, Zinc Oxide.